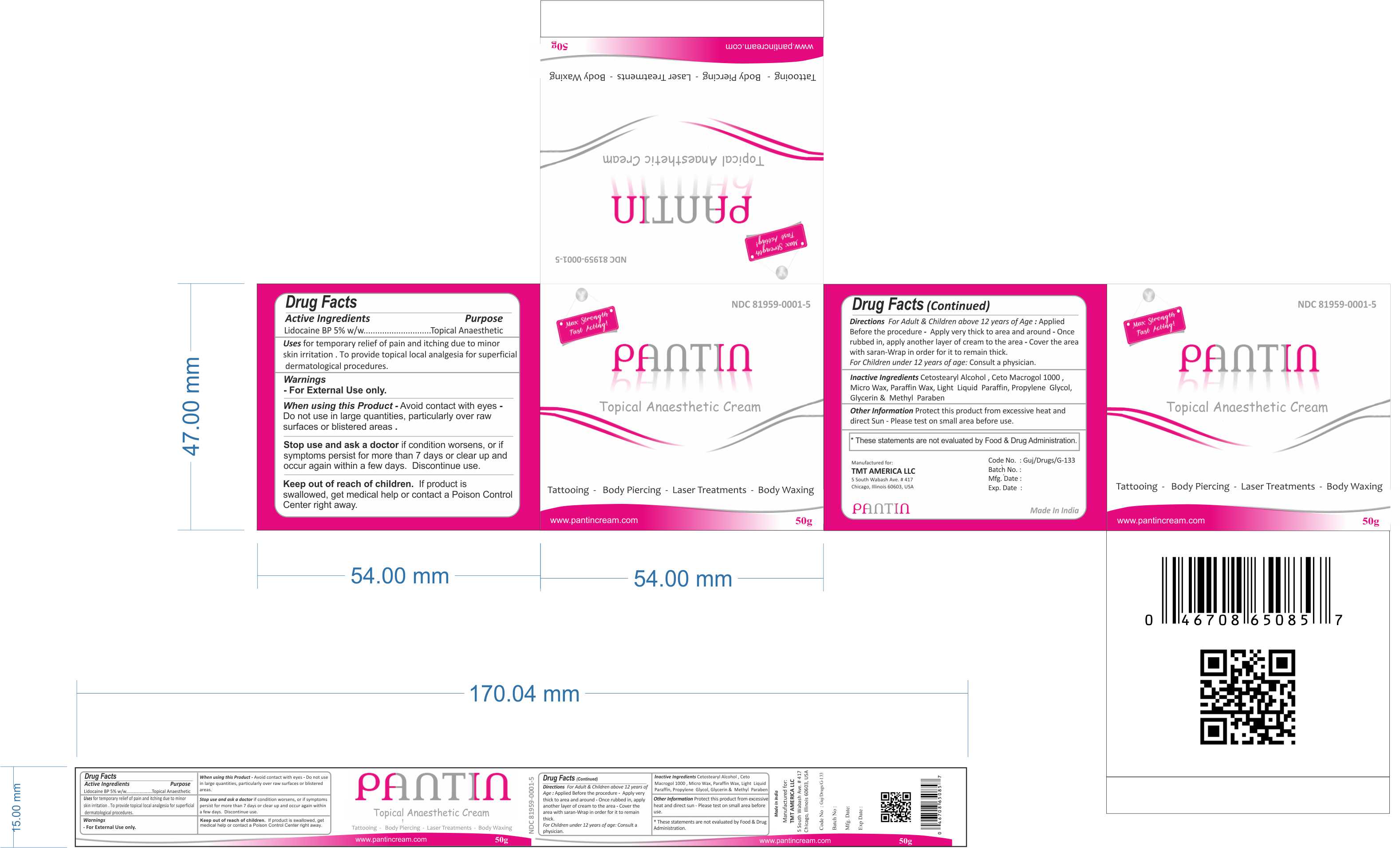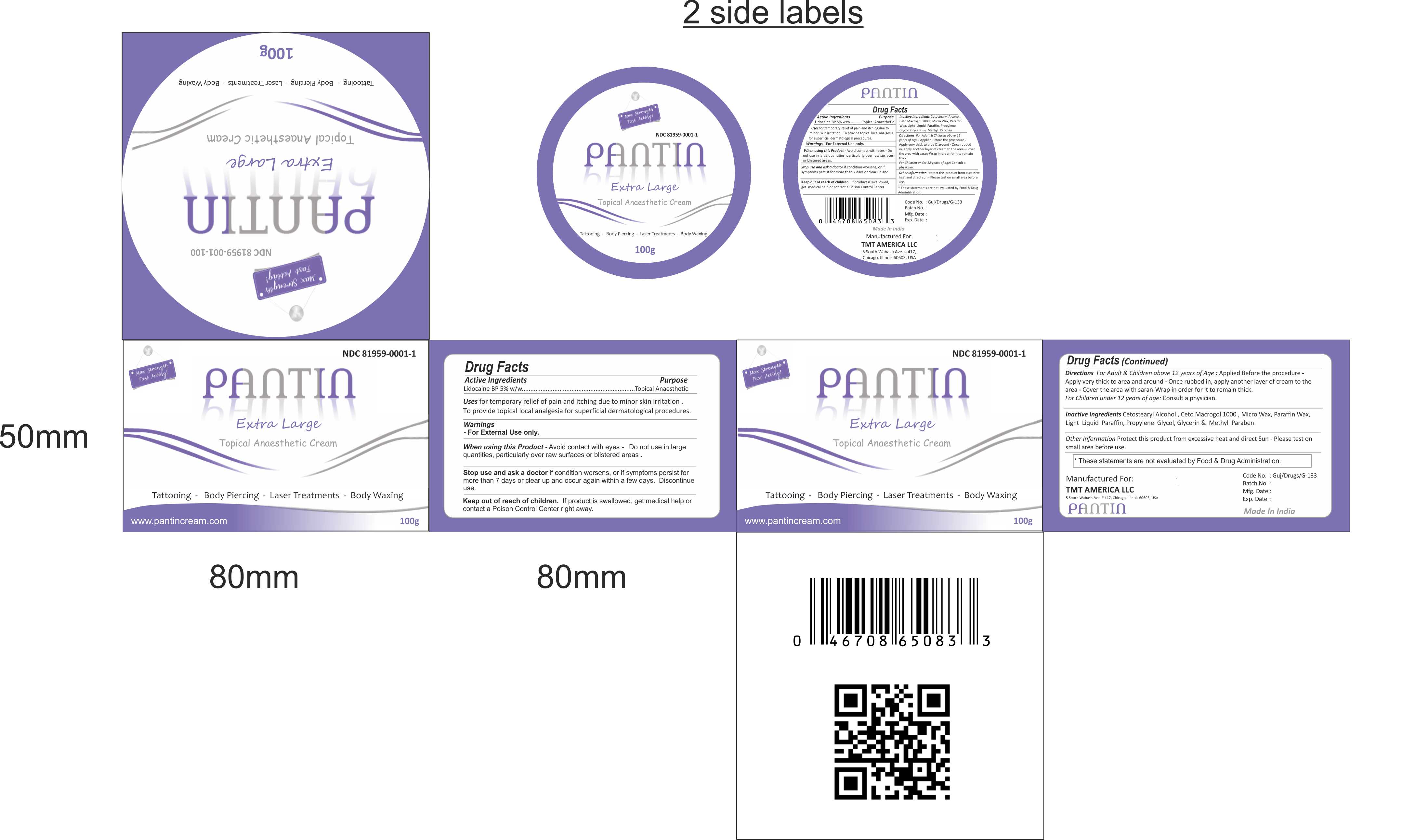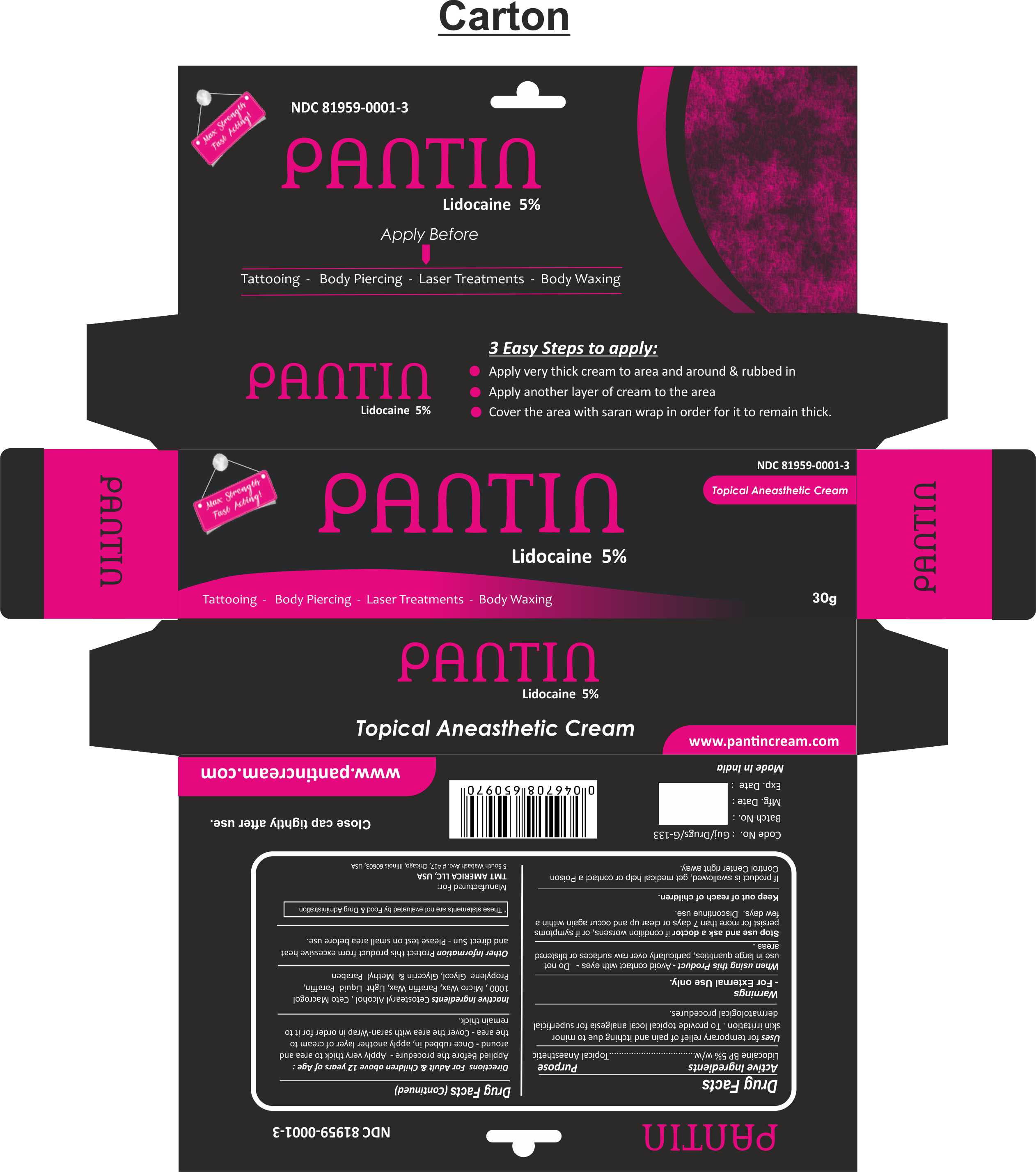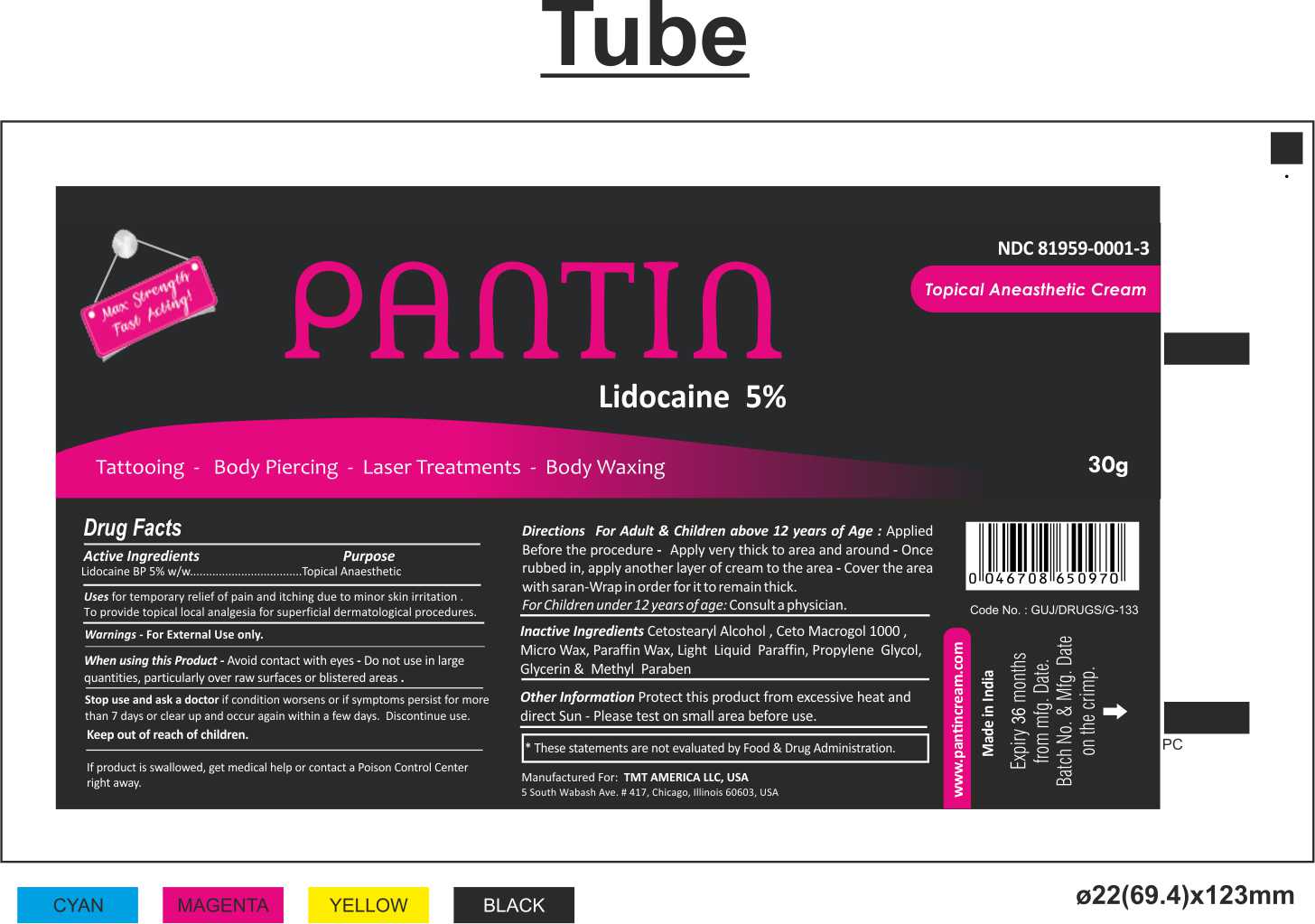 DRUG LABEL: PANTIN
NDC: 81959-0001 | Form: CREAM
Manufacturer: tmt america llc
Category: otc | Type: HUMAN OTC DRUG LABEL
Date: 20211006

ACTIVE INGREDIENTS: LIDOCAINE 2.5 g/50 g
INACTIVE INGREDIENTS: PARAFFIN 1.575 g/50 g; METHYLPARABEN 0.075 g/50 g; WATER 34.025 g/50 g; LIQUID PETROLEUM 4.65 g/50 g; POLYETHYLENE GLYCOL 1000 0.9 g/50 g; MICROCRYSTALLINE WAX 1.275 g/50 g; GLYCERIN 0.5 g/50 g; CETYL ALCOHOL 3.5 g/50 g; PROPYLENE GLYCOL 1 g/50 g

ACTIVE INGREDIENTS:

Lidocaine BP 5%w/w

PURPOSE:

Topical Anaesthetic

INDICATIONS & USAGE

Uses for temporary relief of pain and itching due to minor skin irritation . To provide topical local analgesia for superficial

dermatological procedures.

WARNING:

- For External Use only.

When using this Product - Avoid contact with eyes - Do not use in large quantities, particularly over raw surfaces or blistered areas .

Stop use and ask a doctor if condition worsens, or if symptoms persist for more than 7 days or clear up and occur again within a few days. Discontinue use.

Keep out of reach of children. If product is swallowed, get medical help or contact a Poison Control Center right away.

DIRECTIONS FOR USE:

Directions For Adult & Children above 12 years of Age :

· Applied Before the procedure

· Apply very thick to area and around - Once rubbed in

· apply another layer of cream to the area - Cover the area with saran-Wrap in order for it to remain thick.

For Children under 12 years of age: Consult a physician.

INACTIVE INGREDIENTS:

Cetostearyl Alcohol , Ceto Macrogol 1000 , Micro Wax, Paraffin Wax, Light Liquid Paraffin, Propylene Glycol, Glycerin & Methyl Paraben

OTHER INFROMATIONS:

Protect this product from excessive heat and direct Sun - Please test on small area before use.

* These statements are not evaluated by Food & Drug Administration.